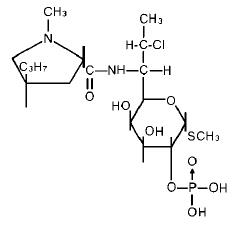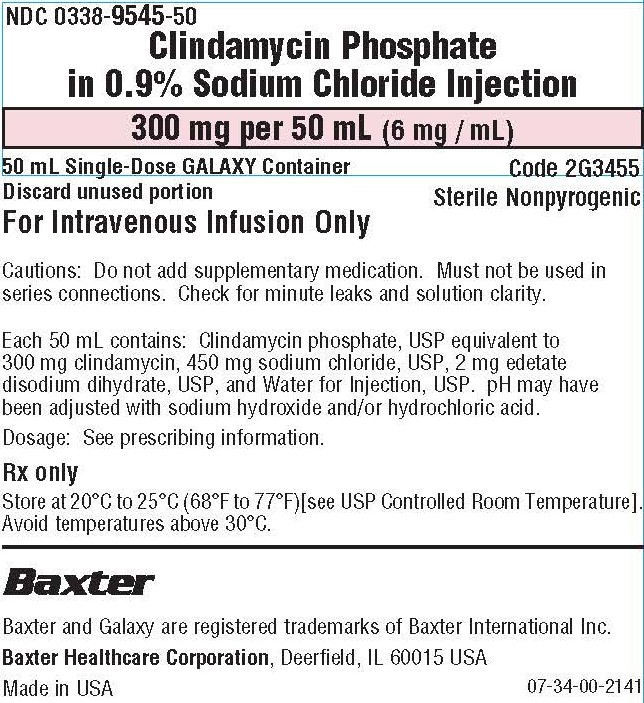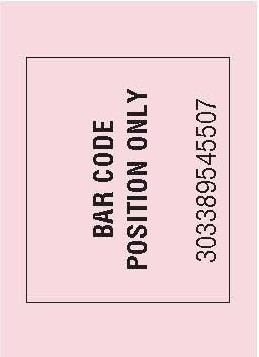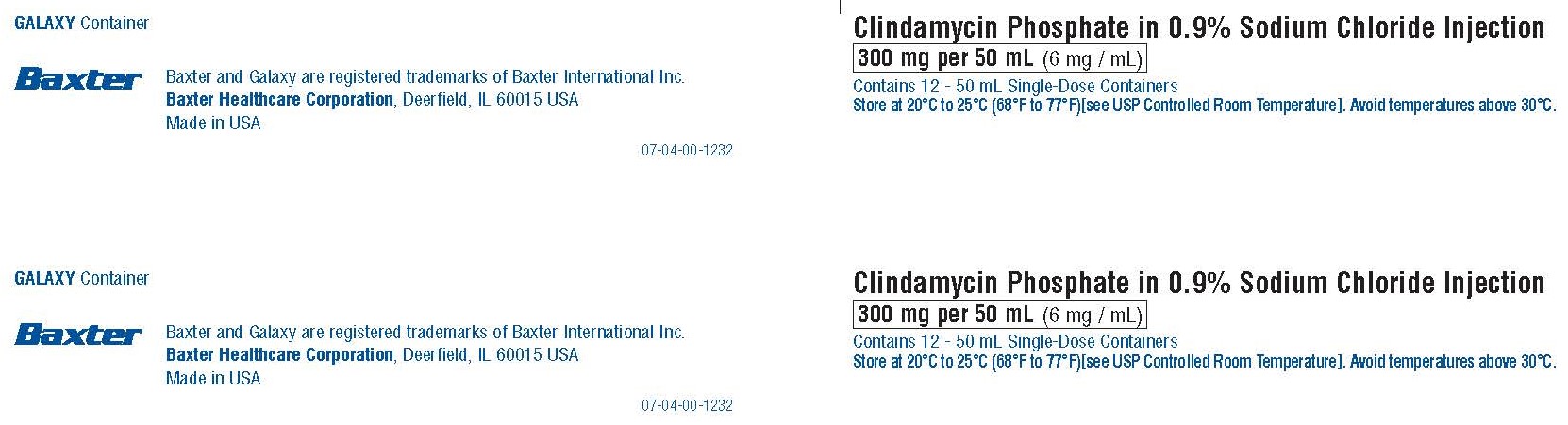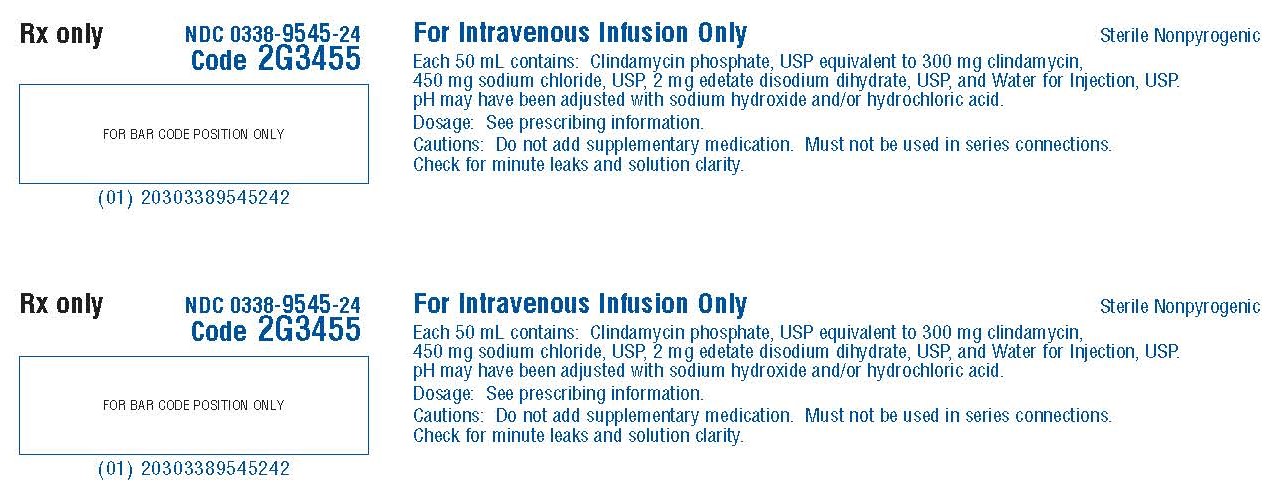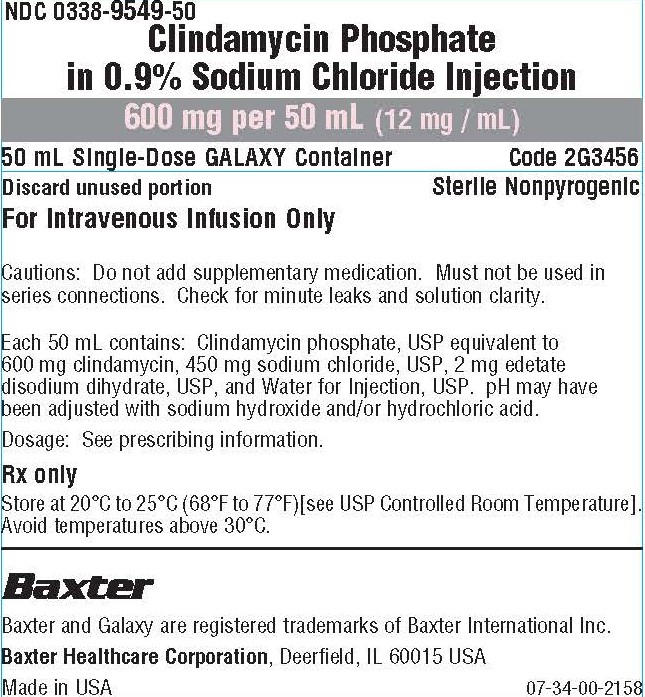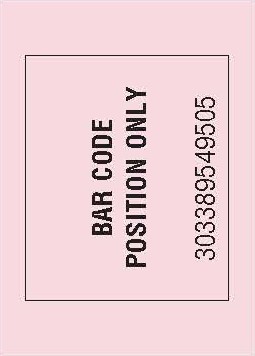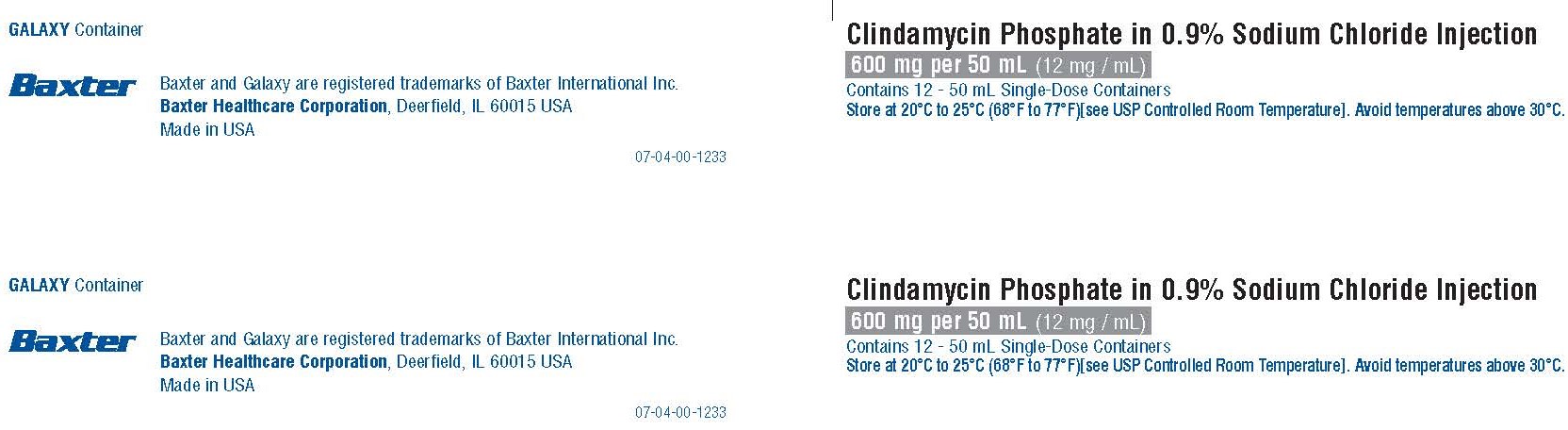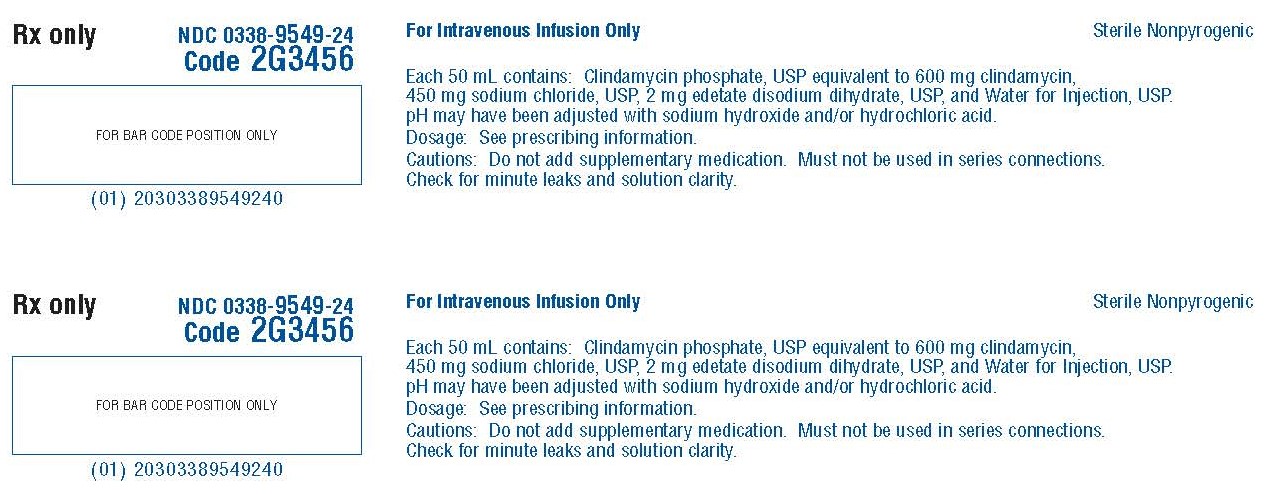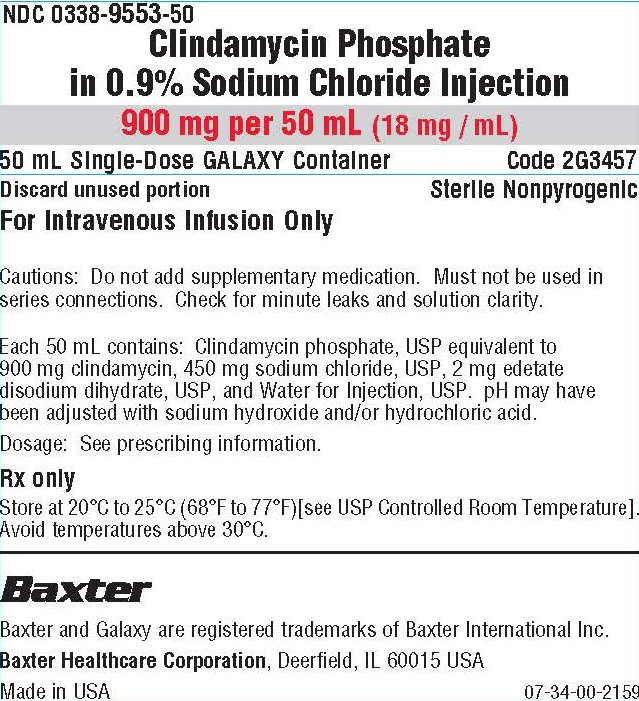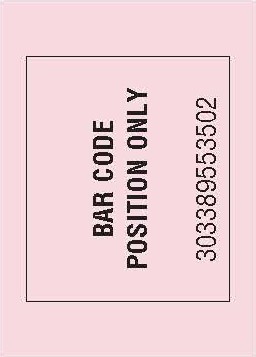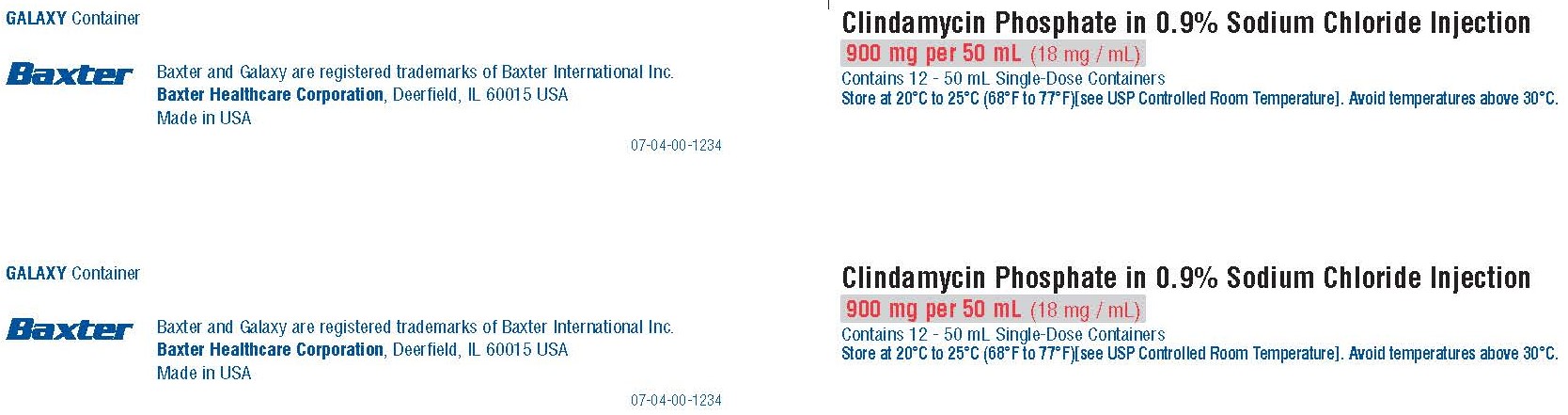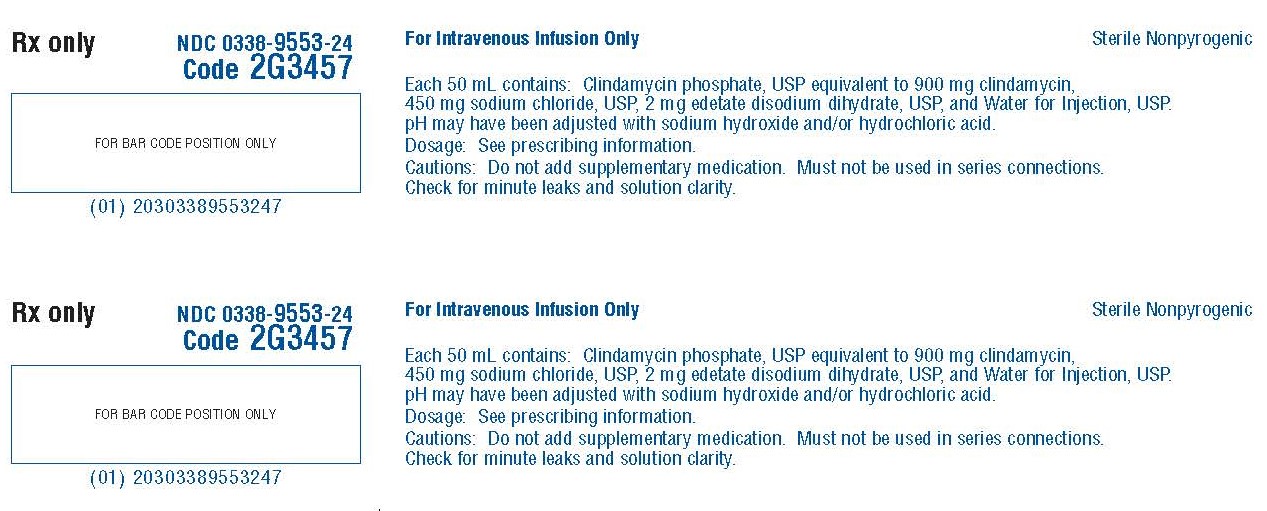 DRUG LABEL: clindamycin phosphate
NDC: 0338-9545 | Form: INJECTION, SOLUTION
Manufacturer: Baxter Healthcare Company
Category: prescription | Type: HUMAN PRESCRIPTION DRUG LABEL
Date: 20250228

ACTIVE INGREDIENTS: CLINDAMYCIN PHOSPHATE 300 mg/50 mL
INACTIVE INGREDIENTS: EDETATE DISODIUM 2.00 mg/50 mL; SODIUM CHLORIDE 450 mg/50 mL; SODIUM HYDROXIDE; HYDROCHLORIC ACID; WATER

HIGHLIGHTS OF PRESCRIBING INFORMATION

These highlights do not include all the information needed to use CLINDAMYCIN PHOSPHATE IN SODIUM CHLORIDE injection safely and effectively. See full prescribing information for CLINDAMYCIN PHOSPHATE IN SODIUM CHLORIDE injection.
CLINDAMYCIN PHOSPHATE IN SODIUM CHLORIDE injection, for intravenous use
Initial U.S. Approval: 1989

RECENT MAJOR CHANGES

Dosage and Administration (2) 9/2022
Warnings and Precautions (5) 9/2022

WARNING: CLOSTRIDIOIDES DIFFICILE-ASSOCIATED DIARRHEA (CDAD) and COLITIS

See full prescribing information for complete boxed warning.

Clostridioides difficile-associated diarrhea (CDAD) has been reported with use of nearly all antibacterial agents, including Clindamycin Phosphate in Sodium Chloride Injection and may range in severity from mild diarrhea to fatal colitis. Treatment with antibacterial agents alters the normal flora of the colon leading to overgrowth of C. difficile (5.1).

Because Clindamycin Phosphate in Sodium Chloride Injection therapy has been associated with severe colitis which may end fatally, it should be reserved for serious infections where less toxic antimicrobial agents are inappropriate (1). It should not be used in patients with nonbacterial infections such as most upper respiratory tract infections. C. difficile produces toxins A and B which contribute to the development of CDAD. Hypertoxin producing isolates of C. difficile cause increased morbidity and mortality, as these infections can be refractory to antimicrobial therapy and may require colectomy (5.1).

1 INDICATIONS AND USAGE

Clindamycin Phosphate in Sodium Chloride Injection contains clindamycin, a lincosamide antibacterial indicated for the treatment of the following in adult and pediatric patients for whom appropriate dosing with this formulation can be achieved:

- Serious infections caused by susceptible anaerobic bacteria (1.1)
- Infections Due to Susceptible Isolates of Streptococci, Pneumococci and Staphylococci. (1.2)
- Lower Respiratory Tract Infections. (1.3)
- Skin and Skin Structure Infections. (1.4)
- Gynecological Infections. (1.5)
- Intra-abdominal Infections. (1.6)
- Septicemia. (1.7)
- Bone and Joint Infections. (1.8)

Limitation of use
Since clindamycin does not diffuse adequately into the cerebrospinal fluid, Clindamycin Phosphate in Sodium Chloride Injection should not be used in the treatment of meningitis (1.9)

Usage
To reduce the development of drug-resistant bacteria and maintain the effectiveness of Clindamycin Phosphate in Sodium Chloride Injection and other antibacterial drugs, Clindamycin Phosphate in Sodium Chloride Injection should be used only to treat or prevent infections that are proven or strongly suspected to be caused by susceptible bacteria. (1.10)

2 DOSAGE AND ADMINISTRATION

- If a dose of Clindamycin Phosphate in Sodium Chloride Injection is required that does not equal 300 mg 600 mg or 900 mg, this product is not recommended for use and an alternative formulation of clindamycin should be considered. (2.1)
- Recommended Adult Dosage: Serious infections due to aerobic gram-positive cocci and the more susceptible anaerobes (NOT generally including Bacteroides fragilis, Peptococcus species and Clostridioides species other than Clostridium perfringens): 600–1200 mg/day in 2, 3 or 4 equal doses by intravenous infusion. (2.2)
- More severe infections, particularly those due to proven or suspected Bacteroides fragilis, Peptococcus species, or Clostridium species other than Clostridium perfringens: 1200–2700 mg/day in 2, 3 or 4 equal doses by intravenous infusion. (2.2)
- Dosage in Pediatric Patients (1 Month of Age to 16 Years): 20 to 40 mg/kg/day in 3 or 4 equal doses by intravenous infusion. (2.3)
- Alternative Pediatric Patients Dosing: 350 mg/m^2/day for serious infections and 450 mg/m2/day for more severe infections. (2.3)
- Dosage in Neonates (Less than 1 Month of Age): 15 to 20 mg/kg/day in 3 to 4 equal doses by intravenous infusion. (2.3)

3 DOSAGE FORMS AND STRENGTHS

Each 50 mL of Clindamycin Phosphate in Sodium Chloride Injection, 300 mg/50 mL (6 mg/mL), 600 mg/50 mL (12 mg/mL), and 900 mg/50 mL (18 mg/mL) contains 300 mg, 600 mg, or 900 mg clindamycin, respectively (as clindamycin phosphate, USP), in a single-dose GALAXY container. (3)

4 CONTRAINDICATIONS

Individuals with a history of hypersensitivity to preparations containing clindamycin or lincomycin. (4)

5 WARNINGS AND PRECAUTIONS

- Anaphylactic shock, anaphylactic reactions and severe hypersensitivity reactions have been reported. Discontinue treatment if such reactions occur. (5.2)
- Cases with acute kidney injury (AKI) have been reported during treatment with clindamycin. Consider renal function monitoring, particularly in certain patients (e.g., those with pre-existing renal dysfunction). Discontinue treatment, if AKI occurs and no other etiology is identified. (5.3)
- Elderly patients with associated severe illness may have a greater risk of developing adverse reactions from diarrhea. Monitor these patients carefully for change in bowel frequency. (5.4)
- Avoid use of Clindamycin Phosphate in Sodium Chloride Injection in individuals with a history of gastrointestinal disease, particularly colitis. (5.5)
- Avoid use of Clindamycin Phosphate in Sodium Chloride Injection in atopic individuals. (5.6)
- During prolonged therapy, perform periodic liver and kidney function tests and blood counts. (5.7)
- The use of Clindamycin Phosphate in Sodium Chloride Injection may result in overgrowth of nonsusceptible organisms-particularly yeasts. Take appropriate measures, if this occurs. (5.8)

6 ADVERSE REACTIONS

Most common adverse reactions: gastrointestinal (abdominal pain, nausea, vomiting) and hypersensitivity reactions (anaphylaxis, urticaria, skin rash). (6)

To report SUSPECTED ADVERSE REACTIONS, contact Baxter Healthcare at 1-866-888-2472 or the FDA at 1-800-FDA-1088 or www.fda.gov/medwatch.

7 DRUG INTERACTIONS

- Neuromuscular blocking properties that may enhance the action of other neuromuscular blocking agents. (7.1)
- Monitor for adverse reactions when strong CYP3A4 and/or CYP3A5 inhibitors are coadministered with clindamycin. (7.2)
- In the presence of strong CYP3A4 and/or CYP3A5 inducers such as rifampicin, monitor for loss of effectiveness. (7.3)

8 USE IN SPECIFIC POPULATIONS

- Pediatric Use: Appropriate monitoring of organ system functions is desirable. (8.4)
- Geriatric Use: Monitor for development of diarrhea. (8.5)

FULL PRESCRIBING INFORMATION

WARNING: CLOSTRIDIOIDES DIFFICILE-ASSOCIATED DIARRHEA (CDAD) and COLITIS

Clostridioides difficile-associated diarrhea (CDAD) has been reported with use of nearly all antibacterial agents, including Clindamycin Phosphate in Sodium Chloride Injection and may range in severity from mild diarrhea to fatal colitis. Treatment with antibacterial agents alters the normal flora of the colon leading to overgrowth of C. difficile.

Because Clindamycin Phosphate in Sodium Chloride Injection therapy has been associated with severe colitis which may end fatally, it should be reserved for serious infections where less toxic antimicrobial agents are inappropriate [see Indications and Usage (1)]. It should not be used in patients with nonbacterial infections such as most upper respiratory tract infections. C. difficile produces toxins A and B which contribute to the development of CDAD. Hypertoxin producing strains of C. difficile cause increased morbidity and mortality, as these infections can be refractory to antimicrobial therapy and may require colectomy. CDAD must be considered in all patients who present with diarrhea following antibacterial use. Careful medical history is necessary since CDAD has been reported to occur over two months after the administration of antibacterial agents.

If CDAD is suspected or confirmed, ongoing antibacterial use not directed against C. difficile may need to be discontinued. Appropriate fluid and electrolyte management, protein supplementation, antibacterial treatment of C. difficile, and surgical evaluation should be instituted as clinically indicated [see Warnings and Precautions (5.1)].

1 INDICATIONS AND USAGE

1.1 Infections Due to Susceptible Anaerobic Bacteria

Clindamycin Phosphate in Sodium Chloride Injection is indicated for the treatment of serious infections caused by susceptible anaerobic bacteria in adults and pediatric patients for whom appropriate dosing with this formulation can be achieved [see Indications and Usage (1.3 - 1.7)].

1.2 Infections Due to Susceptible Isolates of Streptococci, Pneumococci and Staphylococci

Clindamycin Phosphate in Sodium Chloride Injection is indicated for the treatment of serious infections due to susceptible isolates of streptococci, pneumococci, and staphylococci in adults and pediatric patients for whom appropriate dosing with this formulation can be achieved. Its use should be reserved for penicillin-allergic patients or other patients for whom, in the judgment of the physician, a penicillin is inappropriate. Because of the risk of antibacterial-associated pseudomembranous colitis, [see Boxed Warning], before selecting clindamycin the physician should consider the nature of the infection and the suitability of less toxic alternatives (e.g., erythromycin).

Bacteriologic studies should be performed to determine the causative organisms and their susceptibility to clindamycin.

Indicated surgical procedures should be performed in conjunction with antibacterial therapy.

1.3 Lower Respiratory Tract Infections

Clindamycin Phosphate in Sodium Chloride Injection is indicated for the treatment of serious lower respiratory tract infections including pneumonia, empyema, and lung abscess caused by susceptible isolates of anaerobes, Streptococcus pneumoniae, other streptococci (except E. faecalis), and Staphylococcus aureus in adults and pediatric patients for whom appropriate dosing with this formulation can be achieved.

1.4 Skin and Skin Structure Infections

Clindamycin Phosphate in Sodium Chloride Injection is indicated for the treatment of serious skin and skin structure infections caused by susceptible isolates of Streptococcus pyogenes, Staphylococcus aureus, and anaerobes in adults and pediatric patients for whom appropriate dosing with this formulation can be achieved.

1.5 Gynecological Infections

Clindamycin Phosphate in Sodium Chloride Injection is indicated for the treatment of serious gynecological infections including endometritis, nongonococcal tubo-ovarian abscess, pelvic cellulitis, and postsurgical vaginal cuff infection caused by susceptible anaerobes in adults and pediatric patients for whom appropriate dosing with this formulation can be achieved.

1.6 Intra-abdominal Infections

Clindamycin Phosphate in Sodium Chloride Injection is indicated for the treatment of serious intra-abdominal infections including peritonitis and intra-abdominal abscess caused by susceptible anaerobic organisms in adults and pediatric patients for whom appropriate dosing with this formulation can be achieved.

1.7 Septicemia

Clindamycin Phosphate in Sodium Chloride Injection is indicated for the treatment of serious septicemia caused by susceptible isolates of Staphylococcus aureus, streptococci (except Enterococcus faecalis), and susceptible anaerobes in adults and pediatric patients for whom appropriate dosing with this formulation can be achieved.

1.8 Bone and Joint Infections

Clindamycin Phosphate in Sodium Chloride Injection is indicated for the treatment of serious bone and joint infections including acute hematogenous osteomyelitis caused by susceptible isolates of Staphylococcus aureus and as adjunctive therapy in the surgical treatment of chronic bone and joint infections due to susceptible organisms in adults and pediatric patients for whom appropriate dosing with this formulation can be achieved.

1.9 Limitations of Use

Since clindamycin does not diffuse adequately into the cerebrospinal fluid, Clindamycin Phosphate in Sodium Chloride Injection should not be used in the treatment of meningitis [see Clinical Pharmacology (12.3)].

1.10 Usage

To reduce the development of drug-resistant bacteria and maintain the effectiveness of Clindamycin Phosphate in Sodium Chloride Injection and other antibacterial drugs, Clindamycin Phosphate in Sodium Chloride Injection should be used only to treat or prevent infections that are proven or strongly suspected to be caused by susceptible bacteria. When culture and susceptibility information are available, they should be considered in selecting or modifying antibacterial therapy. In the absence of such data, local epidemiology and susceptibility patterns may contribute to the empiric selection of therapy.

2 DOSAGE AND ADMINISTRATION

2.1 Important Administration and Discontinuation Instructions

If a dose of Clindamycin Phosphate in Sodium Chloride Injection is required that does not equal 300 mg 600 mg or 900 mg, this product is not recommended for use and an alternative formulation of clindamycin should be considered.

Administer Clindamycin Phosphate in Sodium Chloride Injection by intravenous infusion over at least 10 minutes. Infusion rates should NOT exceed 30 mg per minute. The usual infusion rates are described in Table 1.

Table 1: Usual Infusion Rates for the Administration of Clindamycin Phosphate in Sodium Chloride Injection
Dose | Time
300 mg | 10 min
600 mg | 20 min
900 mg | 30 min

Discontinue Clindamycin Phosphate in Sodium Chloride Injection if diarrhea occurs during therapy [see Boxed Warning].

2.2 Recommended Adult Dosage

The recommended dosing regimen for Clindamycin Phosphate in Sodium Chloride Injection is 600-1200 mg/day in 2, 3, or 4 equal doses by intravenous infusion for serious infections due to aerobic gram-positive cocci and the more susceptible anaerobes (NOT generally including Bacteroides fragilis, Peptococcus species and Clostridium species other than Clostridium perfringens).

For more severe infections, particularly those due to proven or suspected Bacteroides fragilis, Peptococcus species, or Clostridium species other than Clostridium perfringens, the recommended dosing regimen is 1200-2700 mg/day in 2, 3, or 4 equal doses by intravenous infusion.

In life-threatening situations, these doses may be increased. Doses of as much as 4800 mg daily have been given intravenously to adults.

Alternatively, drug may be administered in the form of a single rapid infusion of the first dose followed by continuous intravenous infusion as follows:

Table 2: Infusion Rates for the Administration of Clindamycin Injection by Single Rapid Infusion followed by Continuous Intravenous Infusion for the Maintenance of Serum Clindamycin Levels
To maintain serum clindamycin levels | Rapid infusion rate | Maintenance infusion rate
Above 4 mcg/mL | 10 mg/min for 30 min | 0.75 mg/min
Above 5 mcg/mL | 15 mg/min for 30 min | 1.00 mg/min
Above 6 mcg/mL | 20 mg/min for 30 min | 1.25 mg/min

2.3 Dosage in Pediatric Patients

If a dose of Clindamycin Phosphate in Sodium Chloride Injection is required that does not equal 300 mg, 600 mg or 900 mg, this product is not recommended for use and an alternative formulation of clindamycin should be considered. The recommended pediatric dosing regimen of Clindamycin Phosphate in Sodium Chloride Injection is as follows:

Pediatric patients (1 month of age to 16 years old):

The recommended dosage is 20 to 40 mg/kg/day in 3 or 4 equal doses.

The higher doses would be used for more severe infections. As an alternative to dosing on a body weight basis, pediatric patients may be dosed on the basis of square meters body surface: 350 mg/m^2/day for serious infections and 450 mg/m^2/day for more severe infections.

Parenteral therapy may be changed to oral formulations of clindamycin when the condition warrants and at the discretion of the physician.

In cases of β-hemolytic streptococcal infections, treatment should be continued for at least 10 days.

Pediatric Patients (less than 1 month):

The recommended dosage is 15 to 20 mg/kg/day in 3 to 4 equal doses. See Table 3 regarding the dosing regimen for pediatric patients with post-menstrual age (PMA) less than or equal to 32 weeks or greater than 32 weeks to less than or equal to 40 weeks.

Table 3: Dosing Regimens for Pediatric Patients with PMA less than or equal to 32 weeks, or greater than 32 weeks to less than or equal to 40 weeks
PMA (weeks) | Dose (mg/kg) | Dosing Interval (hours)
Less than or equal to 32 | 5 | 8
Greater than or equal to 32 weeks to less than or equal to 40 | 7 | 8

PMA: Post-Menstrual Age

2.4 Directions for Use of Clindamycin Phosphate in Sodium Chloride Injection in GALAXY Plastic Container

Parenteral drug products should be inspected visually for particulate matter and discoloration prior to administration, whenever solution and container permit.

Premixed Clindamycin Phosphate in Sodium Chloride Injection is for intravenous infusion using sterile equipment. Check for minute leaks prior to use by squeezing bag firmly. If leaks are found, discard solution as sterility may be impaired. Do NOT add supplementary medication. Parenteral drug products should be inspected visually for particulate matter and discoloration prior to administration whenever solution and container permit. Do NOT use unless solution is clear and seal is intact.

Do NOT use plastic containers in series connections. Such use could result in air embolism due to residual air being drawn from the primary container before administration of the fluid from the secondary container is complete.

Clindamycin Phosphate in Sodium Chloride Injection should not be injected intravenously undiluted as a bolus, but should be infused over at least 10 minutes.

Preparation for Administration:

1. Suspend container from eyelet support.
2. Remove protector from outlet port at bottom of container.
3. Attach administration set. Refer to complete directions accompanying set.

3 DOSAGE FORMS AND STRENGTHS

Injection: Clindamycin Phosphate in Sodium Chloride Injection is a clear, colorless and sterile solution available in three strengths:

- 300 mg/50 mL (6 mg/mL): Each 50 mL single-dose GALAXY container contains 300 mg clindamycin (as clindamycin phosphate, USP) in 0.9% sodium chloride.
- 600 mg/50 mL (12 mg/mL): Each 50 mL single-dose GALAXY container contains 600 mg clindamycin (as clindamycin phosphate, USP) in 0.9% sodium chloride.
- 900 mg/50 mL (18 mg/mL): Each 50 mL single-dose GALAXY container contains 900 mg clindamycin (as clindamycin phosphate, USP) in 0.9% sodium chloride.

4 CONTRAINDICATIONS

Clindamycin Phosphate in Sodium Chloride Injection is contraindicated in individuals with a history of hypersensitivity to preparations containing clindamycin or lincomycin.

5 WARNINGS AND PRECAUTIONS

5.1 Clostridioides difficile-Associated Diarrhea

Clostridioides difficile-associated diarrhea (CDAD) has been reported with use of nearly all antibacterial agents, including Clindamycin Phosphate in Sodium Chloride Injection, and may range in severity from mild diarrhea to fatal colitis. Treatment with antibacterial agents alters the normal flora of the colon leading to overgrowth of C. difficile.

C. difficile produces toxins A and B which contribute to the development of CDAD. Hypertoxin producing isolates of C. difficile cause increased morbidity and mortality, as these infections can be refractory to antimicrobial therapy and may require colectomy. CDAD must be considered in all patients who present with diarrhea following antibacterial use. Careful medical history is necessary since CDAD has been reported to occur over two months after the administration of antibacterial agents.

If CDAD is suspected or confirmed, ongoing antibacterial use not directed against C. difficile may need to be discontinued. Appropriate fluid and electrolyte management, protein supplementation, antibacterial treatment of C. difficile, and surgical evaluation should be instituted as clinically indicated [see Boxed Warning].

5.2 Anaphylactic and Severe Hypersensitivity Reactions

Anaphylactic shock and anaphylactic reactions have been reported [see Adverse Reactions (6)]. Severe hypersensitivity reactions, including severe skin reactions such as toxic epidermal necrolysis (TEN), drug reaction with eosinophilia and systemic symptoms (DRESS), and Stevens-Johnson syndrome (SJS), some with fatal outcome, have been reported [see Adverse Reactions (6)].

In case of such an anaphylactic or severe hypersensitivity reaction, discontinue treatment permanently and institute appropriate therapy.

A careful inquiry should be made concerning previous sensitivities to drugs and other allergens.

5.3 Nephrotoxicity

Clindamycin is potentially nephrotoxic and cases with acute kidney injury have been reported. Consider monitoring of renal function particularly in patients with pre-existing renal dysfunction or those taking concomitant nephrotoxic drugs. In case of acute kidney injury, discontinue Clindamycin Phosphate in Sodium Chloride Injection when no other etiology is identified [see Adverse Reactions (6)].

5.4 Diarrhea in Elderly Patients with Associated Severe Illness

Elderly patients with associated severe illness may have a greater risk of developing adverse reactions from diarrhea. When clindamycin is indicated in these patients, they should be carefully monitored for change in bowel frequency [see Use in Specific Populations (8.5)].

5.5 Use in Patients with Gastrointestinal Disease

Clindamycin Phosphate in Sodium Chloride Injection products should be avoided in individuals with a history of gastrointestinal disease, particularly colitis.

5.6 Use in Atopic Individuals

Clindamycin Phosphate in Sodium Chloride Injection should be avoided in atopic individuals.

5.7 Laboratory Tests: Monitoring to Assess Safety

During prolonged therapy periodic liver and kidney function tests and blood counts should be performed.

Clindamycin dosage modification is not necessary in patients with renal disease. In patients with moderate to severe liver disease, prolongation of clindamycin half-life has been found. However, it was postulated from studies that when given every eight hours, accumulation should rarely occur.
Therefore, dosage modification in patients with liver disease may not be necessary. However, periodic liver enzyme determinations should be made when treating patients with severe liver disease.

5.8 Overgrowth of Nonsusceptible Organisms

The use of Clindamycin Phosphate in Sodium Chloride Injection may result in overgrowth of nonsusceptible organisms-particularly yeasts. If such infections occur, appropriate measures should be taken as indicated by the clinical situation.

5.9 Development of Drug-Resistant Bacteria

Prescribing Clindamycin Phosphate in Sodium Chloride Injection in the absence of a proven or strongly suspected bacterial infection or a prophylactic indication is unlikely to provide benefit to the patient and increases the risk of the development of drug-resistant bacteria.

6 ADVERSE REACTIONS

The following serious adverse reactions to clindamycin are described below and elsewhere in the labeling:

- Clostridioides difficile-Associated Diarrhea [see Warnings and Precautions (5.1)]
- Anaphylactic and Severe Hypersensitivity Reactions [see Warnings and Precautions (5.2)]
- Nephrotoxicity [see Warnings and Precautions (5.3)]

The following adverse reactions associated with the use of clindamycin were identified in clinical trials or postmarketing reports. Because these reactions were reported voluntarily from a population of uncertain size, it is not always possible to estimate their frequency reliably, or to establish a causal relationship to drug exposure.

Infections and Infestations

Clostridioides difficile colitis

Gastrointestinal

Antibacterial-associated colitis [see Warnings and Precautions (5.1)], pseudomembranous colitis, abdominal pain, nausea, and vomiting. The onset of pseudomembranous colitis symptoms may occur during or after antibacterial treatment [see Warnings and Precautions (5.1)]. An unpleasant or metallic taste has been reported after intravenous administration of the higher doses of clindamycin phosphate.

Hypersensitivity Reactions

Maculopapular rash and urticaria have been observed during drug therapy. Generalized mild to moderate morbilliform-like skin rashes are the most frequently reported of all adverse reactions.

Severe skin reactions such as Toxic Epidermal Necrolysis, some with fatal outcome, have been reported [see Warnings and Precautions (5.2)]. Cases of Acute Generalized Exanthematous Pustulosis (AGEP), erythema multiforme, some resembling Stevens-Johnson syndrome, have been associated with clindamycin. Anaphylactic shock, anaphylactic reaction and hypersensitivity have also been reported [see Warnings and Precautions (5.2)].

Skin and Mucous Membranes

Pruritus, vaginitis, angioedema and rare instances of exfoliative dermatitis have been reported [see Warnings and Precautions (5.2)].

Liver

Jaundice and abnormalities in liver function tests have been observed during clindamycin therapy.

Renal

Acute kidney injury [see Warnings and Precautions (5.3)].

Hematopoietic

Transient neutropenia (leukopenia) and eosinophilia have been reported. Reports of agranulocytosis and thrombocytopenia have been made.

Immune System

Drug reaction with eosinophilia and systemic symptoms (DRESS) cases have been reported.

Local Reactions

Thrombophlebitis has been reported after intravenous infusion. Avoid prolonged use of indwelling intravenous catheters.

Musculoskeletal

Polyarthritis cases have been reported.

Cardiovascular

Cardiopulmonary arrest and hypotension have been reported following too rapid intravenous administration [see Dosage and Administration (2)].

7 DRUG INTERACTIONS

7.1 Neuromuscular Blocking Agents

Clindamycin has been shown to have neuromuscular blocking properties that may enhance the action of other neuromuscular blocking agents. Therefore, it should be avoided in patients receiving such agents.

7.2 Inhibitors of CYP3A4 and CYP3A5

Inhibitors of CYP3A4 and/or CYP3A5 may increase plasma concentrations of clindamycin [see Clinical Pharmacology (12.3)]. Monitor for adverse reactions when strong CYP3A4 and/or CYP3A5 inhibitors are coadministered with clindamycin.

7.3 Inducers of CYP3A4 and CYP3A5

Inducers of CYP3A4 and/or CYP3A5 may reduce plasma concentrations of clindamycin. In the presence of strong CYP3A4 and/or CYP3A5 inducers such as rifampicin, monitor for loss of effectiveness.

8 USE IN SPECIFIC POPULATIONS

8.1 Pregnancy

Risk Summary

In limited published clinical trials with pregnant women, the systemic administration of clindamycin during the second and third trimesters, has not been associated with an increased frequency of major birth defects.

The limited published data on use of clindamycin in pregnant women with exposure during the first trimester are insufficient to inform a drug-associated risk of pregnancy-related adverse outcomes [see Data]. In animal reproduction studies, no evidence of any adverse developmental outcomes was observed when oral or subcutaneous doses of clindamycin were administered to pregnant rats and mice during organogenesis at doses half to twice the highest clinically relevant dose based on body surface area comparison [see Data]. The estimated background risk of major birth defects and miscarriage for the indicated population is unknown. All pregnancies have a background risk of birth defect, loss, or other adverse outcomes. In the U.S. general population, the estimated background risk of major birth defects and miscarriage in clinically recognized pregnancies is 2-4% and 15-20%, respectively.

Data

Human Data

In limited published trials in pregnant women administered clindamycin during the first trimester of pregnancy, there was no difference in the rate of major birth defects reported among in utero exposed infants compared to unexposed infants. From these observational data, it is not possible to draw any conclusions on the rate of specific major birth defects associated with clindamycin. These data cannot definitely establish or exclude any clindamycin-associated risk during pregnancy.

Animal Data

Reproduction studies performed during organogenesis (gestational days 6-15) in pregnant rats and mice that were administered oral doses of clindamycin up to 600 mg/kg/day (twice or equivalent to the highest recommended adult human dose based on a body surface area comparison, respectively) or subcutaneous doses of clindamycin up to 250 mg/kg/day (equivalent to or half the highest recommended adult human dose based on a body surface area comparison, respectively) revealed no evidence of teratogenicity.

8.2 Lactation

Risk Summary

Clindamycin has been reported to appear in breast milk in the range of less than 0.5 to 3.8 mcg/mL at dosages of 150 mg orally to 600 mg intravenously. Clindamycin has the potential to cause adverse effects on the breastfed infant’s gastrointestinal flora.

The developmental and health benefits of breastfeeding should be considered along with the mother's clinical need for clindamycin and any potential adverse effects on the breast-fed child from clindamycin or from the underlying maternal condition.

Clinical Considerations

If oral or intravenous clindamycin is required by a nursing mother, it is not a reason to discontinue breastfeeding, but an alternate drug may be preferred. Monitor the infant for possible adverse effects on the gastrointestinal flora, such as diarrhea, candidiasis (thrush, diaper rash) or blood in the stool indicating possible antibacterial-associated colitis.

8.4 Pediatric Use

Clindamycin Phosphate in Sodium Chloride Injection is indicated for the treatment of serious infections caused by susceptible anaerobic bacteria, infections due to susceptible isolates of streptococci, pneumococci and staphylococci, lower respiratory tract Infections, skin and skin structure infections, gynecological infections, intra-abdominal infections, septicemia and bone and joint infections in pediatric patients for whom appropriate dosing with this formulation can be achieved [see Indications and Usage (1.1-1.8)] and Dosage and Administration (2.3)].

When Clindamycin Phosphate in Sodium Chloride Injection is administered to the pediatric population (less than 1 month to 16 years old) appropriate dosing and monitoring of organ system functions is desirable. Because of the limitations of the available strengths and administration requirements (i.e., administration of fractional doses is not recommended) of Clindamycin Phosphate in Sodium Chloride Injection, and to avoid unintentional overdose, this product is not recommended for use if a dose of Clindamycin Phosphate in Sodium Chloride Injection is required that does not equal 300 mg 600 mg or 900 mg is required and an alternative formulation of clindamycin should be considered [see Dosage and Administration (2.3)].

The potential for the toxic effect in the pediatric population from chemicals that may leach from the single dose premixed Clindamycin Phosphate in Sodium Chloride Injection preparation in plastic has not been evaluated.

8.5 Geriatric Use

Clinical studies of clindamycin did not include sufficient numbers of patients age 65 and over to determine whether they respond differently from younger patients. However, other reported clinical experience indicates that antibacterial-associated colitis and diarrhea (due to Clostridioides difficile) seen in association with most antibacterial drugs occur more frequently in the elderly (>60 years) and may be more severe. These patients should be carefully monitored for the development of diarrhea.

Pharmacokinetic studies with clindamycin have shown no clinically important differences between young and elderly subjects with normal hepatic function and normal (age-adjusted) renal function after oral or intravenous administration [see Clinical Pharmacology (12.3)].

10 OVERDOSAGE

Significant mortality was observed in mice at an intravenous dose of 855 mg/kg (~3 times the human dose based on body surface area) and in rats at an oral or subcutaneous dose of approximately 2618 mg/kg (~18 times the human dose based on body surface area). In the mice, convulsions and depression were observed and in rats depression was observed prior to death.

Hemodialysis and peritoneal dialysis are not effective in removing clindamycin from the serum.

11 DESCRIPTION

Clindamycin Phosphate in Sodium Chloride Injection contains clindamycin phosphate, a water-soluble ester of clindamycin. Clindamycin is a semisynthetic antibacterial produced by a 7(S)-chloro-substitution of the 7(R)-hydroxyl group of the parent antibacterial lincomycin.

The chemical name of clindamycin phosphate is L-threo-α-D-galacto-Octopyranoside, methyl-7-chloro-6,7,8-trideoxy-6-[[(1-methyl-4-propyl-2-pyrrolidinyl)carbonyl]amino]01-thio-, 2-(dihydrogen phosphate), (2S-trans)-.

The molecular formula is C18H34CIN2O8PS and the molecular weight is 504.96.

The structural formula is represented below:

Clindamycin Phosphate in Sodium Chloride Injection is a clear, colorless and sterile solution for intravenous infusion available in three strengths, 300 mg/50 mL, 600 mg/50 mL, and 900 mg/50 mL, containing 300 mg, 600 mg or 900 mg clindamycin, respectively (as clindamycin phosphate, USP). Each 50 mL of all the strengths of Clindamycin Phosphate in Sodium Chloride Injection also contains, 450 mg of sodium chloride USP, 2 mg of edetate disodium dihydrate USP, and water for Injection USP. The pH is adjusted with sodium hydroxide and /or hydrochloric acid. Clindamycin Phosphate in Sodium Chloride Injection is filled in GALAXY plastic container fabricated from a specially designed multilayer plastic. Solutions in contact with the plastic container can leach out certain of its chemical components in very small amounts within the expiration period. The suitability of the plastic has been confirmed in tests in animals according to the USP biological tests for plastic containers, as well as by tissue culture toxicity studies.

12 CLINICAL PHARMACOLOGY

12.1 Mechanism of Action

Clindamycin is an antibacterial drug [see Microbiology (12.4)].

12.3 Pharmacokinetics

Clindamycin phosphate is a water-soluble ester prodrug of clindamycin. Biologically inactive clindamycin phosphate is converted to active clindamycin. By the end of short-term intravenous infusion, peak serum concentrations of active clindamycin are reached.

After intramuscular injection of clindamycin phosphate, peak concentrations of active clindamycin are reached within 3 hours in adults and 1 hour in pediatric patients. Serum concentration-time curves may be constructed from intravenous peak serum concentrations by application of elimination half-lives described in the elimination section below.

Serum concentrations of clindamycin can be maintained above the in vitro minimum inhibitory concentrations for most indicated organisms by administration of clindamycin phosphate every 8 to 12 hours in adults and every 6 to 8 hours in pediatric patients, or by continuous intravenous infusion. An equilibrium state is reached by the third dose.

Distribution

No significant concentrations of clindamycin are attained in the cerebrospinal fluid even in the presence of inflamed meninges.

Elimination

Clindamycin is metabolized predominantly by CYP3A4, and to a lesser extent by CYP3A5, to the major metabolite clindamycin sulfoxide and minor metabolite N-desmethylclindamycin. Biologically inactive clindamycin phosphate disappears from the serum with 6 minutes of the average elimination half-life; however, the average serum elimination half-life of active clindamycin is about 3 hours in adults and 2.5 hours in pediatric patients.

Specific Populations

Patients with Renal/Hepatic Impairment

The elimination half-life of clindamycin is increased slightly in patients with markedly reduced renal or hepatic function. Hemodialysis and peritoneal dialysis are not effective in removing clindamycin from the serum. Dosage schedules do not need to be modified in patients with renal or hepatic disease.

Geriatric Patients

Pharmacokinetic studies in elderly volunteers (61-79 years) and younger adults (18-39 years) indicate that age alone does not alter clindamycin pharmacokinetics (clearance, elimination half-life, volume of distribution, and area under the serum concentration-time curve) after intravenous administration of clindamycin phosphate. After oral administration of clindamycin hydrochloride, the average elimination half-life is increased to approximately 4.0 hours (range 3.4-5.1 h) in the elderly, compared to 3.2 hours (range 2.1-4.2 h) in younger adults. The extent of absorption, however, is not different between age groups and no dosage alteration is necessary for the elderly with normal hepatic function and normal (age-adjusted) renal function^1.

Pharmacokinetics in Pediatric Patients with PMA ≤ 32 weeks, or > 32 to ≤ 40 weeks

Systemic clearance (CL) in premature infants increases with increases in bodyweight (kg) and post-menstrual age (PMA). The dosing regimens for pediatric patients ≤ 32 weeks PMA (5 mg/kg) and 32 to ≤ 40 weeks PMA (7 mg/kg), both administered IV every 8 hours, achieve exposures comparable to therapeutic exposures in adults (weighing 70 kg) administered clindamycin 600 mg every 8 hours (Table 4).

Table 4: Predicted Drug Exposure (Mean ± SD) of Clindamycin in Adults and in Pediatric Patients with PMA ≤ 32 weeks, or > 32 to ≤ 40 weeks
Age | Adult (70 kg) | PMA ≤ 32 weeks | PMA > 32 - ≤ 40 weeks
Dose (every 8 hours) | 600 mg | 5 mg/kg | 7 mg/kg
AUCss,0-8hour (mcg.h/mL) | 50.5 (30.9) | 52.5 (17.0) | 55.9 (23.6)
Cmax,ss (mcg/mL) | 12.0 (3.5) | 9.0 (2.2) | 10.5 (2.8)
Cmin,ss (mcg/mL) | 3.1 (3.3) | 4.6 (2.0) | 4.4 (2.8)

PMA: post-menstrual age; AUCss,0-8 hour: area under the concentration-time curve during a dosing interval at steady state; Cmax,ss: maximum drug concentration at steady state; Cmin,ss: minimum or trough drug concentration at steady state

Obese Pediatric Patients Aged 2 to Less than 18 Years and Obese Adults Aged 18 to 20 Years

An analysis of pharmacokinetic data in obese pediatric patients aged 2 to less than 18 years and obese adults aged 18 to 20 years demonstrated that clindamycin clearance and volume of distribution, normalized by total body weight, are comparable regardless of obesity.

Drug Interaction Studies

In vitro studies indicate that clindamycin does not inhibit CYP1A2, CYP2C9, CYP2C19, CYP2E1 or CYP2D6 and only moderately inhibits CYP3A4.

12.4 Microbiology

Mechanism of Action

Clindamycin inhibits bacterial protein synthesis by binding to the 23S RNA of the 50S subunit of the ribosome. Clindamycin is bacteriostatic.

Resistance

Resistance to clindamycin is most often caused by modification of specific bases of the 23S ribosomal RNA. Cross-resistance between clindamycin and lincomycin is complete. Because the binding sites for these antibacterial drugs overlap, cross-resistance is sometimes observed among lincosamides, macrolides and streptogramin B. Macrolide-inducible resistance to clindamycin occurs in some isolates of macrolide-resistant bacteria. Macrolide-resistant isolates of staphylococci and beta-hemolytic streptococci should be screened for induction of clindamycin resistance using the D-zone test.

Antimicrobial Activity

Clindamycin has been shown to be active against most isolates of the following microorganisms, both in vitro and in clinical infections [see Indications and Usage (1)].

Aerobic bacteria
Gram-positive bacteria
  Staphylococcus aureus (methicillin-susceptible isolates)
  Streptococcus pneumoniae (penicillin-susceptible isolates)
  Streptococcus pyogenes
Anaerobic bacteria
Gram-positive bacteria
  Clostridium perfringens
  Peptostreptococcus anaerobius
  Gram-negative bacteria
  Fusobacterium necrophorum
  Fusobacterium nucleatum
  Prevotella melaninogenica

The following in vitro data are available, but their clinical significance is unknown. At least 90 percent of the following bacteria exhibit an in vitro minimum inhibitory concentration (MIC) less than or equal to the susceptible breakpoint for clindamycin against isolates of similar genus or organism group. However, the efficacy of clindamycin in treating clinical infections caused by these bacteria has not been established in adequate and well-controlled clinical trials.

Aerobic bacteria
Gram-positive bacteria
  Staphylococcus epidermidis (methicillin-susceptible isolates)
  Streptococcus agalactiae
  Streptococcus anginosus
  Streptococcus mitis
  Streptococcus oralis
Anaerobic bacteria
Gram-positive bacteria
  Actinomyces israelii
  Clostridium clostridioforme
  Eggerthella lenta
  Finegoldia (Peptostreptococcus) magna
  Micromonas (Peptostreptococcus) micros
  Cutibacterium acnes
  Gram-negative bacteria
  Prevotella bivia
  Prevotella intermedia

Susceptibility Testing

For specific information regarding susceptibility test interpretive criteria, and associated test methods and quality control standards recognized by FDA for this drug, please see https://www.fda.gov/STIC.

13 NONCLINICAL TOXICOLOGY

13.1 Carcinogenesis, Mutagenesis, Impairment of Fertility

Long term studies in animals have not been performed with clindamycin to evaluate carcinogenic potential. Genotoxicity tests performed included a rat micronucleus test and an Ames Salmonella reversion test. Both tests were negative.

Fertility studies in rats treated orally with up to 300 mg/kg/day (approximately 1.1 times the highest recommended adult human dose based on mg/m^2) revealed no effects on fertility or mating ability.

15 REFERENCES

1. Smith RB, Phillips JP: Evaluation of CLEOCIN HCl and CLEOCIN Phosphate in an Aged Population. Upjohn TR 8147-82-9122-021, December 1982.

16 HOW SUPPLIED/STORAGE AND HANDLING

Clindamycin Phosphate in Sodium Chloride Injection is a clear, colorless and sterile solution for intravenous infusion. Each 50 mL of Clindamycin in Phosphate in Sodium Chloride Injection, 300 mg/50 mL, 600mg/50mL, and 900 mg/50 mL, contains 300 mg, 600 mg, or 900 mg clindamycin, respectively (as clindamycin phosphate, USP) in 0.9% sodium chloride solution. Clindamycin in Phosphate in Sodium Chloride Injection in single-dose GALAXY containers is available as follows:

2G3455 | Twenty-four (24)-300 mg/50 mL containers | NDC 0338-9545-24
2G3456 | Twenty-four (24)-600 mg/50 mL containers | NDC 0338-9549-24
2G3457 | Twenty-four (24)-900 mg/50 mL containers | NDC 0338-9553-24

Exposure of pharmaceutical products, including clindamycin phosphate in sodium chloride, to heat should be minimized. It is recommended that GALAXY plastic containers be stored at 20°C to 25°C (68°F to 77°F) excursions permitted to 15°C to 30°C (59°F to 86°F) [see USP Controlled Room Temperature]. Avoid temperatures above 30°C.

17 PATIENT COUNSELING INFORMATION

C. difficile-Associated Diarrhea (CDAD)

Advise patients that diarrhea is a common problem caused by antibacterial drugs including Clindamycin Phosphate in Sodium Chloride Injection, that usually ends when the antibacterial is discontinued. Sometimes after starting treatment with antibacterial drugs, including Clindamycin Phosphate in Sodium Chloride Injection, patients can develop watery and bloody stools (with or without stomach cramps and fever) even as late as two or more months after having taken the last dose of the antibacterial drugs. If this occurs, contact physician as soon as possible [see Warnings and Precautions (5.1)].

Antibacterial Resistance

Patients should be counseled that antibacterial drugs including Clindamycin Phosphate in Sodium Chloride Injection should only be used to treat bacterial infections. They do not treat viral infections (e.g., the common cold). When Clindamycin Phosphate in Sodium Chloride Injection is prescribed to treat a bacterial infection, patients should be told that although it is common to feel better early in the course of therapy, the medication should be taken exactly as directed. Skipping doses or not completing the full course of therapy may (1) decrease the effectiveness of the immediate treatment and (2) increase the likelihood that bacteria will develop resistance and will not be treatable by Clindamycin Phosphate in Sodium Chloride Injection or other antibacterial drugs in the future.

Lactation

Advise a woman to monitor the breastfed infant for diarrhea and bloody stools [see Use in Specific Populations (8.2)].

Baxter Healthcare Corporation
Deerfield, IL 60015 USA

Made in USA.

Baxter and Galaxy are registered trademarks of Baxter International Inc.

07-19-09-273

PACKAGE/LABEL PRINCIPAL DISPLAY PANEL

Container Label

NDC 0338-9545-50
Clindamycin Phosphate
in 0.9% Sodium Chloride Injection
300 mg per 50 mL (6 mg / mL)

50 mL Single-Dose GALAXY Container
Code 2G3455

Discard unused portion
Sterile Nonpyrogenic

For Intravenous Infusion Only

Cautions: Do not add supplementary medication. Must not be used in
series connections. Check for minute leaks and solution clarity.

Each 50 mL contains: Clindamycin phosphate, USP equivalent to
300 mg clindamycin, 450 mg sodium chloride, USP, 2 mg edetate
disodium dihydrate, USP, and Water for Injection, USP. pH may have
been adjusted with sodium hydroxide and/or hydrochloric acid.

Dosage: See prescribing information.

Rx only
Store at 20°C to 25°C (68°F to 77°F)[see USP Controlled Room Temperature].
Avoid temperatures above 30°C.

BAXTER Logo

Baxter and Galaxy are registered trademarks of Baxter International Inc.
Baxter Healthcare Corporation, Deerfield, IL 60015 USA
Made in USA

07-34-00-2141

Bar Code Position Only
303389545507

Carton Label

GALAXY Container

BAXTER Logo

Baxter and Galaxy are registered trademarks of Baxter International Inc.
Baxter Healthcare Corporation, Deerfield, IL 60015 USA
Made in USA

07-04-00-1232

Clindamycin Phosphate in 0.9% Sodium Chloride Injection
300 mg per 50 mL (6 mg / mL)
Contains 12 - 50 mL Single-Dose Containers
Store at 20°C to 25°C (68°F to 77°F) [see USP Controlled Room Temperature]. Avoid temperatures above 30°C.

Rx only
NDC 0338-9545-24
Code 2G3455

FOR BAR CODE POSITION ONLY
(01) 20303389545242

For Intravenous Infusion Only
Sterile Nonpyrogenic

Each 50 mL contains: Clindamycin phosphate, USP equivalent to 300 mg clindamycin,
450 mg sodium chloride, USP, 2 mg edetate disodium dihydrate, USP, and Water for Injection, USP.
pH may have been adjusted with sodium hydroxide and/or hydrochloric acid.
Dosage: See prescribing information.
Cautions: Do not add supplementary medication. Must not be used in series connections.
Check for minute leaks and solution clarity.

Container Label

NDC 0338-9549-50
Clindamycin Phosphate
in 0.9% Sodium Chloride Injection

600 mg per 50 mL (12 mg / mL)

50 mL Single-Dose GALAXY Container
Code 2G3456

Discard unused portion
For Intravenous Use Only

Sterile Nonpyrogenic

Cautions: Do not add supplementary medication. Must not be used in
series connections. Check for minute leaks and solution clarity.

Each 50 mL contains: Clindamycin phosphate, USP equivalent to
600 mg clindamycin, 450 mg sodium chloride, USP, 2 mg edetate
disodium dihydrate, USP, and Water for Injection, USP. pH may have
been adjusted with sodium hydroxide and/or hydrochloric acid.

Dosage: See prescribing information.

Rx only
Store at 20° to 25°C (68° to 77°F) [see USP Controlled Room Temperature].
Avoid temperatures above 30°C.

BAXTER Logo

Baxter and Galaxy are registered trademarks of Baxter International Inc.
Baxter Healthcare Corporation, Deerfield, IL 60015 USA
Made in USA

07-34-00-2158

BAR CODE POSTION ONLY
303389549505

Carton Label

GALAXY Container

BAXTER Logo

Baxter and Galaxy are registered trademarks of Baxter International Inc.
Baxter Healthcare Corporation, Deerfield, IL 60015 USA
Made in USA

07-04-00-1233

Clindamycin Phosphate in 0.9% Sodium Chloride Injection
600 mg per 50 mL (12 mg / mL)
Contains 12 - 50 mL Single-Dose Containers
Store at 20°C to 25°C (68°F to 77°F)[see USP Controlled Room Temperature]. Avoid temperatures above 30°C.

Rx only
NDC 0338-9549-24
Code 2G3456

FOR BAR CODE POSITION ONLY
(01) 20303389549240

For Intravenous Infusion Only
Sterile Nonpyrogenic

Each 50 mL contains: Clindamycin phosphate, USP equivalent to 600 mg clindamycin,
450 mg sodium chloride, USP, 2 mg edetate disodium dihydrate, USP, and Water for Injection, USP.
pH may have been adjusted with sodium hydroxide and/or hydrochloric acid.
Dosage: See prescribing information.
Cautions: Do not add supplementary medication. Must not be used in series connections.
Check for minute leaks and solution clarity.

Container Label

NDC 0338-9553-50
Clindamycin Phosphate in 0.9% Sodium Chloride Injection

900 mg per 50 mL (18 mg / mL)

50 mL Single-Dose GALAXY Container
Code 2G3457
Discard unused portion
Sterile Nonpyrogenic
For Intravenous Infusion Only

Cautions: Do not add supplementary medication. Must not be used in
series connections. Check for minute leaks and solution clarity.

Each 50 mL contains: Clindamycin phosphate, USP equivalent to
900 mg clindamycin, 450 mg sodium chloride, USP, 2 mg edetate
disodium dihydrate, USP, and Water for Injection, USP. pH may have
been adjusted with sodium hydroxide and/or hydrochloric acid.
Dosage: See prescribing information.

Rx only
Store at 20° to 25°C (68° to 77°F) [see USP Controlled Room Temperature].
Avoid temperatures above 30°C.

BAXTER Logo

Baxter and Galaxy are registered trademarks of Baxter International Inc.
Baxter Healthcare Corporation, Deerfield, IL 60015 USA
Made in USA

07-34-00-2159

BAR CODE POSITION ONLY
303389553502

Carton Label

GALAXY Container

BAXTER Logo

Baxter and Galaxy are registered trademarks of Baxter International Inc.
Baxter Healthcare Corporation, Deerfield, IL 60015 USA
Made in USA

07-04-00-1234

Clindamycin Phosphate in 0.9% Sodium Chloride Injection
900 mg per 50 mL (18 mg / mL)
Contains 12 - 50 mL Single-Dose Containers
Store at 20°C to 25°C (68°F to 77°F)[see USP Controlled Room Temperature]. Avoid temperatures above 30°C.

Rx only
NDC 0338-9553-24
Code 2G3457

FOR BAR CODE POSITION ONLY
(01) 20303389553247

For Intravenous Infusion Only
Sterile Nonpyrogenic

Each 50 mL contains: Clindamycin phosphate, USP equivalent to 900 mg clindamycin,
450 mg sodium chloride, USP, 2 mg edetate disodium dihydrate, USP, and Water for Injection, USP.
pH may have been adjusted with sodium hydroxide and/or hydrochloric acid.
Dosage: See prescribing information.
Caution: Do not add supplementary medication. Must not be used in series connections.
Check for minute leaks and solution clarity.